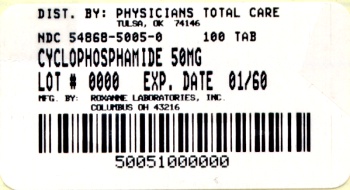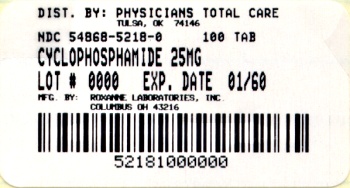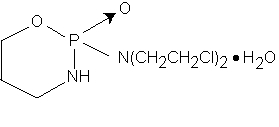 DRUG LABEL: Cyclophosphamide
NDC: 54868-5218 | Form: TABLET
Manufacturer: Physicians Total Care, Inc.
Category: prescription | Type: HUMAN PRESCRIPTION DRUG LABEL
Date: 20120123

ACTIVE INGREDIENTS: CYCLOPHOSPHAMIDE 25 mg/1 1
INACTIVE INGREDIENTS: ACACIA; FD&C BLUE NO. 1; LACTOSE MONOHYDRATE; MAGNESIUM STEARATE; CELLULOSE, MICROCRYSTALLINE

CYCLOPHOSPHAMIDE Tablets USP, 25 mg and 50 mg

DESCRIPTION

Cyclophosphamide is a synthetic antineoplastic drug chemically related to the nitrogen mustards. Cyclophosphamide is a white crystalline powder with the molecular formula C7H15Cl2N2O2P • H2O and a molecular weight of 279.1. The chemical name for cyclophosphamide is 2H-1,3,2-Oxazaphosphorin-2-amine, N,N-bis(2-chloroethyl)tetrahydro-, 2-oxide, monohydrate, (±). Cyclophosphamide is soluble in water, saline, or ethanol and has the following structural formula:

Each tablet for oral administration contains cyclophosphamide (anhydrous) 25 mg or 50 mg. In addition, each tablet contains the following inactive ingredients: acacia, FD&C Blue No. 1, lactose monohydrate, magnesium stearate, and microcrystalline cellulose.

CLINICAL PHARMACOLOGY

Cyclophosphamide is biotransformed principally in the liver to active alkylating metabolites by a mixed function microsomal oxidase system. These metabolites interfere with the growth of susceptible rapidly proliferating malignant cells. The mechanism of action is thought to involve cross-linking of tumor cell DNA.

Cyclophosphamide is well absorbed after oral administration with a bioavailability greater than 75%. The unchanged drug has an elimination half-life of 3 to 12 hours. It is eliminated primarily in the form of metabolites, but from 5% to 25% of the dose is excreted in urine as unchanged drug. Several cytotoxic and noncytotoxic metabolites have been identified in urine and in plasma. Concentrations of metabolites reach a maximum in plasma 2 to 3 hours after an intravenous dose. Plasma protein binding of unchanged drug is low but some metabolites are bound to an extent greater than 60%. It has not been demonstrated that any single metabolite is responsible for either the therapeutic or toxic effects of cyclophosphamide. Although elevated levels of metabolites of cyclophosphamide have been observed in patients with renal failure, increased clinical toxicity in such patients has not been demonstrated.

INDICATIONS AND USAGE

Malignant Diseases

Cyclophosphamide Tablets USP, 25 mg and 50 mg, although effective alone in susceptible malignancies, are more frequently used concurrently or sequentially with other antineoplastic drugs. The following malignancies are often susceptible to cyclophosphamide treatment:

1. Malignant lymphomas (Stages III and IV of the Ann Arbor staging system), Hodgkin’s disease, lymphocytic lymphoma (nodular or diffuse), mixed-cell type lymphoma, histiocytic lymphoma, Burkitt’s lymphoma.
2. Multiple myeloma.
3. Leukemias: Chronic lymphocytic leukemia, chronic granulocytic leukemia (it is usually ineffective in acute blastic crisis), acute myelogenous and monocytic leukemia, acute lymphoblastic (stem-cell) leukemia in children (cyclophosphamide given during remission is effective in prolonging its duration).
4. Mycosis fungoides (advanced disease).
5. Neuroblastoma (disseminated disease).
6. Adenocarcinoma of the ovary.
7. Retinoblastoma.
8. Carcinoma of the breast.

Nonmalignant Disease

Biopsy Proven “Minimal Change” Nephrotic Syndrome in Children:

Cyclophosphamide Tablets USP, 25 mg and 50 mg are useful in carefully selected cases of biopsy proven “minimal change” nephrotic syndrome in children but should not be used as primary therapy. In children whose disease fails to respond adequately to appropriate adrenocorticosteroid therapy or in whom the adrenocorticosteroid therapy produces or threatens to produce intolerable side effects, cyclophosphamide may induce a remission. Cyclophosphamide is not indicated for the nephrotic syndrome in adults or for any other renal disease.

CONTRAINDICATIONS

Continued use of cyclophosphamide is contraindicated in patients with severely depressed bone marrow function. Cyclophosphamide is contraindicated in patients who have demonstrated a previous hypersensitivity to it (see WARNINGS and PRECAUTIONS).

WARNINGS

Carcinogenesis, Mutagenesis, and Impairment of Fertility

Second malignancies have developed in some patients treated with cyclophosphamide used alone or in association with other antineoplastic drugs and/or modalities. Most frequently, they have been urinary bladder, myeloproliferative, or lymphoproliferative malignancies. Second malignancies most frequently were detected in patients treated for primary myeloproliferative or lymphoproliferative malignancies or nonmalignant disease in which immune processes are believed to be involved pathologically.

In some cases, the second malignancy developed several years after cyclophosphamide treatment had been discontinued. In a single breast cancer trial utilizing two to four times the standard dose of cyclophosphamide in conjunction with doxorubicin a small number of cases of secondary acute myeloid leukemia occurred within two years of treatment initiation. Urinary bladder malignancies generally have occurred in patients who previously had hemorrhagic cystitis. In patients treated with cyclophosphamide-containing regimens for a variety of solid tumors, isolated case reports of secondary malignancies have been published. One case of carcinoma of the renal pelvis was reported in a patient receiving long-term cyclophosphamide therapy for cerebral vasculitis. The possibility of cyclophosphamide-induced malignancy should be considered in any benefit-to-risk assessment for use of the drug.

Cyclophosphamide can cause fetal harm when administered to a pregnant woman and such abnormalities have been reported following cyclophosphamide therapy in pregnant women. Abnormalities were found in two infants and a six-month-old fetus born to women treated with cyclophosphamide. Ectrodactylia was found in two of the three cases. Normal infants have also been born to women treated with cyclophosphamide during pregnancy, including the first trimester. If this drug is used during pregnancy, or if the patient becomes pregnant while taking (receiving) this drug, the patient should be apprised of the potential hazard to the fetus. Women of childbearing potential should be advised to avoid becoming pregnant.

Cyclophosphamide interferes with oogenesis and spermatogenesis. It may cause sterility in both sexes. Development of sterility appears to depend on the dose of cyclophosphamide, duration of therapy, and the state of gonadal function at the time of treatment. Cyclophosphamide-induced sterility may be irreversible in some patients.

Amenorrhea associated with decreased estrogen and increased gonadotropin secretion develops in a significant proportion of women treated with cyclophosphamide. Affected patients generally resume regular menses within a few months after cessation of therapy. Girls treated with cyclophosphamide during prepubescence generally develop secondary sexual characteristics normally and have regular menses. Ovarian fibrosis with apparently complete loss of germ cells after prolonged cyclophosphamide treatment in late prepubescence has been reported. Girls treated with cyclophosphamide during prepubescence subsequently have conceived.

Men treated with cyclophosphamide may develop oligospermia or azoospermia associated with increased gonadotropin but normal testosterone secretion. Sexual potency and libido are unimpaired in these patients. Boys treated with cyclophosphamide during prepubescence develop secondary sexual characteristics normally, but may have oligospermia or azoospermia and increased gonadotropin secretion. Some degree of testicular atrophy may occur. Cyclophosphamide-induced azoospermia is reversible in some patients, though the reversibility may not occur for several years after cessation of therapy. Men temporarily rendered sterile by cyclophosphamide have subsequently fathered normal children.

Urinary System

Hemorrhagic cystitis may develop in patients treated with cyclophosphamide. Rarely, this condition can be severe and even fatal. Fibrosis of the urinary bladder, sometimes extensive, also may develop with or without accompanying cystitis. Atypical urinary bladder epithelial cells may appear in the urine. These adverse effects appear to depend on the dose of cyclophosphamide and the duration of therapy. Such bladder injury is thought to be due to cyclophosphamide metabolites excreted in the urine. Forced fluid intake helps to assure an ample output of urine, necessitates frequent voiding, and reduces the time the drug remains in the bladder. This helps to prevent cystitis. Hematuria usually resolves in a few days after cyclophosphamide treatment is stopped, but it may persist. Medical and/or surgical supportive treatment may be required, rarely, to treat protracted cases of severe hemorrhagic cystitis. It is usually necessary to discontinue cyclophosphamide therapy in instances of severe hemorrhagic cystitis.

Cardiac Toxicity

Although a few instances of cardiac dysfunction have been reported following use of recommended doses of cyclophosphamide, no causal relationship has been established. Acute cardiac toxicity has been reported with doses as low as 2.4 g/m^2 to as high as 26 g/m^2, usually as a portion of an intensive antineoplastic multi-drug regimen or in conjunction with transplantation procedures. In a few instances with high doses of cyclophosphamide, severe, and sometimes fatal, congestive heart failure has occurred after the first cyclophosphamide dose. Histopathologic examination has primarily shown hemorrhagic myocarditis. Hemopericardium has occurred secondary to hemorrhagic myocarditis and myocardial necrosis. Pericarditis has been reported independent of any hemopericardium.

No residual cardiac abnormalities, as evidenced by electrocardiogram or echocardiogram appear to be present in patients surviving episodes of apparent cardiac toxicity associated with high doses of cyclophosphamide.

Cyclophosphamide has been reported to potentiate doxorubicin-induced cardiotoxicity.

Infections

Treatment with cyclophosphamide may cause significant suppression of immune responses. Serious, sometimes fatal, infections may develop in severely immunosuppressed patients. Cyclophosphamide treatment may not be indicated, or should be interrupted, or the dose reduced, in patients who have or who develop viral, bacterial, fungal, protozoan, or helminthic infections.

Other

Anaphylactic reactions have been reported; death has also been reported in association with this event. Possible cross-sensitivity with other alkylating agents has been reported.

PRECAUTIONS

General

Special attention to the possible development of toxicity should be exercised in patients being treated with cyclophosphamide if any of the following conditions are present:

1. Leukopenia
2. Thrombocytopenia
3. Tumor cell infiltration of bone marrow
4. Previous X-ray therapy
5. Previous therapy with other cytotoxic agents
6. Impaired hepatic function
7. Impaired renal function

Laboratory Tests

During treatment, the patient’s hematologic profile (particularly neutrophils and platelets) should be monitored regularly to determine the degree of hematopoietic suppression. Urine should also be examined regularly for red cells which may precede hemorrhagic cystitis.

Drug Interactions

The rate of metabolism and the leukopenic activity of cyclophosphamide reportedly are increased by chronic administration of high doses of phenobarbital.

The physician should be alert for possible combined drug actions, desirable or undesirable, involving cyclophosphamide even though cyclophosphamide has been used successfully concurrently with other drugs, including other cytotoxic drugs.

Cyclophosphamide treatment, which causes a marked and persistent inhibition of cholinesterase activity, potentiates the effect of succinylcholine chloride.

If a patient has been treated with cyclophosphamide within 10 days of general anesthesia, the anesthesiologist should be alerted.

Adrenalectomy

Since cyclophosphamide has been reported to be more toxic in adrenalectomized dogs, adjustment of the doses of both replacement steroids and cyclophosphamide may be necessary for the adrenalectomized patient.

Wound Healing

Cyclophosphamide may interfere with normal wound healing.

Carcinogenesis, Mutagenesis, and Impairment of Fertility

See WARNINGS: Carcinogenesis, Mutagenesis, and Impairment of Fertility.

Pregnancy

Pregnancy Category D:

See WARNINGS.

Nursing Mothers

Cyclophosphamide is excreted in breast milk. Because of the potential for serious adverse reactions and the potential for tumorigenicity shown for cyclophosphamide in humans, a decision should be made whether to discontinue nursing or to discontinue the drug, taking into account the importance of the drug to the mother.

Pediatric Use

The safety profile of cyclophosphamide in pediatric patients is similar to that of the adult population (see ADVERSE REACTIONS).

Geriatric Use

Insufficient data from clinical studies of cyclophospamide for malignant lymphoma, multiple myeloma, leukemia, mycosis fungoides, neuroblastoma, retinoblastoma, and breast carcinoma are available for patients 65 years of age and older to determine whether they respond differently than younger patients. In two clinical trials in which cyclophosphamide was compared with paclitaxel, each in combination with cisplatin, for the treatment of advanced ovarian carcinoma, 154 (28%) of 552 patients who received cyclophosphamide plus cisplatin were 65 years or older. Subset analyses (<65 versus >65 years) from these trials, published reports of clinical trials of cyclophosphamide-containing regimens in breast cancer and non-Hodgkin’s lymphoma, and postmarketing experience suggest that elderly patients may be more susceptible to cyclophosphamide toxicities. In general, dose selection for an elderly patient should be cautious, usually starting at the low end of the dosing range and adjusting as necessary based on patient response (see DOSAGE AND ADMINISTRATION: Treatment of Malignant Diseases).

ADVERSE REACTIONS

Information on adverse reactions associated with the use of cyclophosphamide is arranged according to body system affected or type of reaction. The adverse reactions are listed in order of decreasing incidence. The most serious adverse reactions are described in the WARNINGS section.

Reproductive System

See WARNINGS: Carcinogenesis, Mutagenesis, and Impairment of Fertility.

Digestive System

Nausea and vomiting commonly occur with cyclophosphamide therapy. Anorexia and, less frequently, abdominal discomfort or pain and diarrhea may occur. There are isolated reports of hemorrhagic colitis, oral mucosal ulceration and jaundice occurring during therapy. These adverse drug effects generally remit when cyclophosphamide treatment is stopped.

Skin and Its Structures

Alopecia occurs commonly in patients treated with cyclophosphamide. The hair can be expected to grow back after treatment with the drug or even during continued drug treatment, though it may be different in texture or color. Skin rash occurs occasionally in patients receiving the drug. Pigmentation of the skin and changes in nails can occur. Very rare reports of Stevens-Johnson syndrome and toxic epidermal necrolysis have been received during postmarketing surveillance; due to the nature of spontaneous adverse event reporting, a definitive causal relationship to cyclophosphamide has not been established.

Hematopoietic System

Leukopenia occurs in patients treated with cyclophosphamide, is related to the dose of drug, and can be used as a dosage guide. Leukopenia of less than 2000 cells/mm^3 develops commonly in patients treated with an initial loading dose of the drug, and less frequently in patients maintained on smaller doses. The degree of neutropenia is particularly important because it correlates with a reduction in resistance to infections. Fever without documented infection has been reported in neutropenic patients.

Thrombocytopenia or anemia develop occasionally in patients treated with cyclophosphamide. These hematologic effects usually can be reversed by reducing the drug dose or by interrupting treatment. Recovery from leukopenia usually begins in 7 to 10 days after cessation of therapy.

Urinary System

See WARNINGS: Urinary System for information on cystitis and urinary bladder fibrosis.

Hemorrhagic ureteritis and renal tubular necrosis have been reported to occur in patients treated with cyclophosphamide. Such lesions usually resolve following cessation of therapy.

Infections

See WARNINGS: Infections for information on reduced host resistance to infections.

Carcinogenesis

See WARNINGS: Carcinogenesis, Mutagenesis, and Impairment of Fertility.

Respiratory System

Interstitial pneumonitis has been reported as part of the postmarketing experience. Interstitial pulmonary fibrosis has been reported in patients receiving high doses of cyclophosphamide over a prolonged period.

Other

Anaphylactic reactions have been reported; death has also been reported in association with this event. Possible cross-sensitivity with other alkylating agents has been reported. SIADH (syndrome of inappropriate ADH secretion) has been reported with the use of cyclophosphamide. Malaise and asthenia have been reported as part of the postmarketing experience.

OVERDOSAGE

No specific antidote for cyclophosphamide is known. Overdosage should be managed with supportive measures, including appropriate treatment for any concurrent infection, myelosuppression, or cardiac toxicity should it occur.

DOSAGE AND ADMINISTRATION

Treatment of Malignant Diseases

Adults and Children:

Oral cyclophosphamide dosing is usually in the range of 1 to 5 mg/kg/day for both initial and maintenance dosing.

Many other regimens of intravenous and oral cyclophosphamide have been reported. Dosages must be adjusted in accord with evidence of antitumor activity and/or leukopenia. The total leukocyte count is a good, objective guide for regulating dosage. Transient decreases in the total white blood cell count to 2000 cells/mm^3 (following short courses) or more persistent reduction to 3000 cells/mm^3 (with continuing therapy) are tolerated without serious risk of infection if there is no marked granulocytopenia.

When cyclophosphamide is included in combined cytotoxic regimens, it may be necessary to reduce the dose of cyclophosphamide, as well as that of the other drugs.

Cyclophosphamide and its metabolites are dialyzable although there are probably quantitative differences depending upon the dialysis system being used. Patients with compromised renal function may show some measurable changes in pharmacokinetic parameters of cyclophosphamide metabolism, but there is no consistent evidence indicating a need for cyclophosphamide dosage modification in patients with renal function impairment.

Treatment of Nonmalignant Diseases

Biopsy Proven “Minimal Change” Nephrotic Syndrome in Children:

An oral dose of 2.5 to 3 mg/kg daily for a period of 60 to 90 days is recommended. In males, the incidence of oligospermia and azoospermia increases if the duration of cyclophosphamide treatment exceeds 60 days. Treatment beyond 90 days increases the probability of sterility. Adrenocorticosteroid therapy may be tapered and discontinued during the course of cyclophosphamide therapy (see PRECAUTIONS: Laboratory Tests).

Preparation and Handling of Solutions

Extemporaneous liquid preparations of cyclophosphamide for oral administration may be prepared by dissolving cyclophosphamide for injection in Aromatic Elixir, N.F. Such preparations should be stored under refrigeration in glass containers and used within 14 days.

HOW SUPPLIED

Cyclophosphamide Tablets USP

25 mg, light blue, round, unscored tablets

(Identified 54 639)

NDC 54868-5218-0: Bottle of 100 tablets

NDC 54868-5218-1: Bottle of 10 tablets.

50 mg, light blue, round, unscored tablets

(Identified 54 980)

NDC 54868-5005-0: Bottle of 100 tablets.

Storage

Storage at or below 25°C (77°F) is recommended; this product will withstand brief exposure to temperatures up to 30°C (86°F) but should be protected from temperatures above 30°C (86°F).

Procedures for proper handling and disposal of anticancer drugs should be considered. Several guidelines on this subject have been published.^1-8 There is no general agreement that all of the procedures recommended in the guidelines are necessary or appropriate.

To minimize the risk of dermal exposure, always wear impervious gloves when handling bottles containing cyclophosphamide tablets. This includes all handling activities in clinical settings, pharmacies, storerooms, and home healthcare settings, including during unpacking and inspection, transport within a facility, and dose preparation and administration.

References

1. ONS Clinical Practice Committee. Cancer Chemotherapy Guidelines and Recommendations for Practice. Pittsburgh, PA: Oncology Nursing Society; 1999:32-41.
2. Recommendations for the safe handling of parenteral antineoplastic drugs. Washington, DC: Division of Safety, National Institutes of Health; 1983. US Dept of Health and Human Services, Public Health Service publication NIH 83-2621.
3. AMA Council on Scientific Affairs. Guidelines for handling parenteral antineoplastics. JAMA.1985; 253: 1590-1592.
4. National Study Commission on Cytotoxic Exposure. Recommendations for handling cytotoxic agents. 1987. Available from Louis P. Jeffrey, Chairman, National Study Commission on Cytotoxic Exposure. Massachusetts College of Pharmacy and Allied Health Sciences, 179 Longwood Avenue, Boston, MA 02115.
5. Clinical Oncological Society of Australia. Guidelines and recommendations for safe handling of antineoplastic agents. Med J Aust.1983;1:426-428.
6. Jones RB, Frank R, Mass T. Safe handling of chemotherapeutic agents: a report from The Mount Sinai Medical Center. CA Cancer J Clin.1983;33:258-263.
7. American Society of Hospital Pharmacists. ASHP technical assistance bulletin on handling cytotoxic and hazardous drugs. Am J Hosp Pharm.1990;47:1033-1049.
8. Controlling occupational exposure to hazardous drugs. (OSHA Work-Practice Guidelines.) Am J Health- Syst Pharm.1996;53:1669-1685.

4047201//03

Revised September 2007

© RLI, 2007

Relabeling and Repackaging by:
Physicians Total Care, Inc.
Tulsa, Oklahoma 74146

Package Label - Cyclophosphamide Tablets USP

25 mg

CYTOTOXIC AGENT

Rx Only

50 mg

CYTOTOXIC AGENT

Rx Only